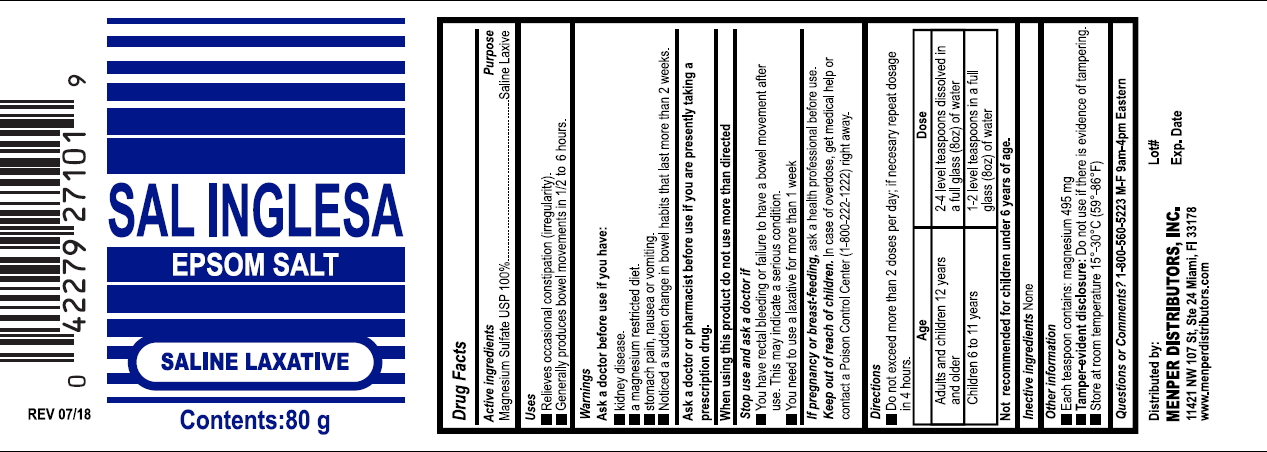 DRUG LABEL: Sal Inglesa
NDC: 53145-580 | Form: CRYSTAL
Manufacturer: Menper Distributors, Inc
Category: otc | Type: HUMAN OTC DRUG LABEL
Date: 20250701

ACTIVE INGREDIENTS: MAGNESIUM SULFATE HEPTAHYDRATE 1 g/1 g

Sal Inglesa (EPSOM SALT)

Active Ingredient & Purposes

Active ingredient | Purpose
Magensium sulfate heptahydrate 100%.................................... | Laxative

Uses

For relief of occasional constipation (irregularity). Generally produces bowel movement in ½ to 6 hours.

Warnings

Do not use

- laxative products for more than 1 week unless directed

Ask a doctor before use if you have

- kidney disease
- a magnesium-restricted diet
- stomach pain, nausea, or vomiting
- noticed a sudden change in bowel habits that last more than 2 weeks

Stop use and ask a doctor if

- You have rectal bleeding or
- Fail to have a bowel movement after use. This may indicate a serious condition.
- You need to use a laxative for more than a week

If pregnant or breast-feeding

ask a health professional before use.

Keep this and all drugs out of reach of children.

In case of overdose, get medical help or contact a Poison Control Center (1-800-222-1222) right away.

Directions

- tbsp = tablespoon
- drink a full glass (8 ounces) of liquid with each dose. The dose may be taken as a single daily dose or in divided doses.
- do not exceed maximum daily dosage, unless directed by a doctor

adults and children 12 years of age and older | 2-4 level teaspoons dissolved in a full glass (8oz) of water
children 6 to under 12 years of age | 1-2 level teaspoons dissolved in a full glass (8oz) of water
children under 6 years of age | Not recomended

Other information

- each teaspoon (5g) contains: magnesium 495 mg
- do not use if there is evidence of tampering.
- store between 15-30°C (59-86°F)

Inactive ingredient

None

Questions?

+1-800-56035223 (M-F)9 AM - 4 PM EST Eastern